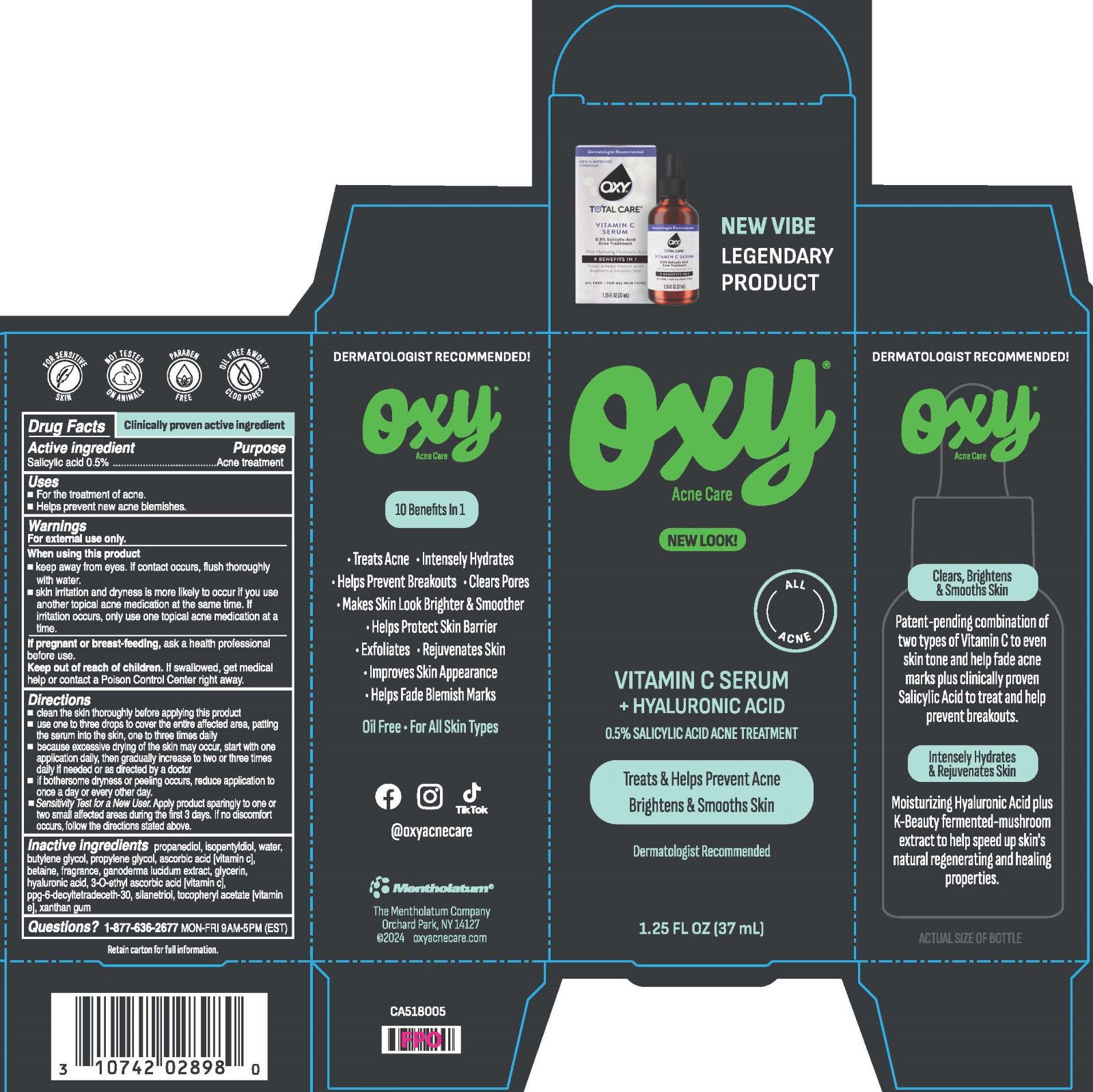 DRUG LABEL: Oxy Vitamin C Serum
NDC: 10742-1005 | Form: LIQUID
Manufacturer: The Mentholatum Company
Category: otc | Type: HUMAN OTC DRUG LABEL
Date: 20241226

ACTIVE INGREDIENTS: SALICYLIC ACID 5 mg/1 mL
INACTIVE INGREDIENTS: GLYCERIN; BUTYLENE GLYCOL; DECYLTETRADECETH-30; ISOPENTYLDIOL; XANTHAN GUM; WATER; SILANETRIOL; FRAGRANCE 13576; HYALURONIC ACID; DIPROPYLENE GLYCOL; BETAINE; GANODERMA LUCIDUM STEM; ASCORBIC ACID; 3-O-ETHYL ASCORBIC ACID; PROPANEDIOL; ALPHA-TOCOPHEROL ACETATE

Drug Facts - Oxy Oxy Vitamin C Serum + Hyaluronic Acid

Active ingredient

Salicylic acid 0.5%

Purpose

Acne treatment

Uses

- For the treatment of acne
- Helps prevent new acne blemishes

Warnings

For external use only.

When using this product

- keep away from eyes. If contact occurs, flush thoroughly with water.
- skin irritation and dryness is more likely to occur if you use another topical acne medication at the same time. If irritation occurs, only use one topical acne medication at a time.

If pregnant or breast-feeding,

ask a health professional before use.

Keep Out of Reach of Children

If swallowed, get medical help or contact a Poison Control Center right away.

Directions

- clean the skin thoroughly before applying this product
- use one to three drops to cover the entire affected area, patting the serum into the skin, one to three times daily.
- because excessive drying of the skin may occur, start with one application daily, then gradually increase to two or three times daily if needed or as directed by a doctor
- if bothersome dryness or peeling occurs, reduce application to once a day or every other day.

Sensitivity Test for a New User. Apply product sparingly to one or two small affected areas during the first 3 days. If no discomfort occurs, follow the directions stated above.

Inactive ingredients

propanediol, isopentyldiol, water, butylene glycol, propylene glycol, ascorbic acid [vitamin C], betaine, fragrance, ganoderma lucidum extract, glycerin, hyaluronic acid, 3-O-ethyl ascorbic acid [vitamin C], PPG-6-Decyltetradeceth-30, silanetriol, tocopheryl acetate [Vitamin E], xanthan gum

Questions?

1-877-636-2677 MON-FRI 9AM-5PM (EST)